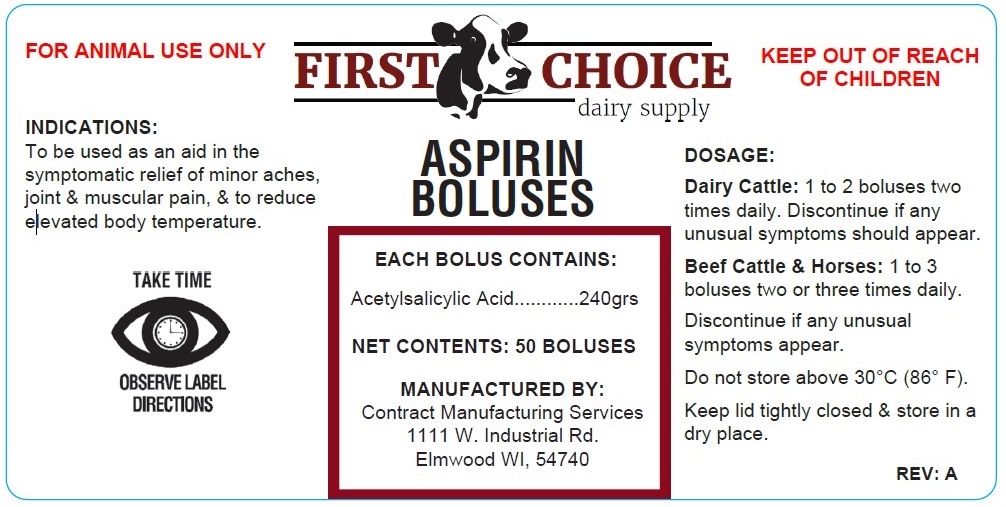 DRUG LABEL: FIRST CHOICE dairy supply ASPIRIN BOLUS
NDC: 86158-2085 | Form: TABLET
Manufacturer: Contract Manufacturing Services, LLC
Category: animal | Type: OTC ANIMAL DRUG LABEL
Date: 20240821

ACTIVE INGREDIENTS: ASPIRIN 16 g/1 1
INACTIVE INGREDIENTS: STARCH, CORN

FIRST CHOICE dairy supply ASPIRIN BOLUSES

EACH BOLUS CONTAINS:

Acetylsalicylic Acid............240grs

DOSAGE:

Dairy Cattle: 1 to 2 boluses two times daily. Discontinue if any unusual symptoms should appear.

Beef Cattle & Horses: 1 to 3 boluses two or three times daily.

Discontinue if any unusual symptoms appear.

STORAGE AND HANDLING

Do not store above 30°C (86° F).

Keep lid tightly closed & store in a dry place.

INDICATIONS:

To be used as an aid in the symptomatic relief of minor aches, joint & muscular pain, & to reduce elevated body temperature.

KEEP OUT OF REACH OF CHILDREN

FOR ANIMAL USE ONLY

TAKE TIME

OBSERVE LABEL DIRECTIONS

MANUFACTURED BY:
Contract Manufacturing Services
1111 W. Industrial Rd.
Elmwood WI, 54740